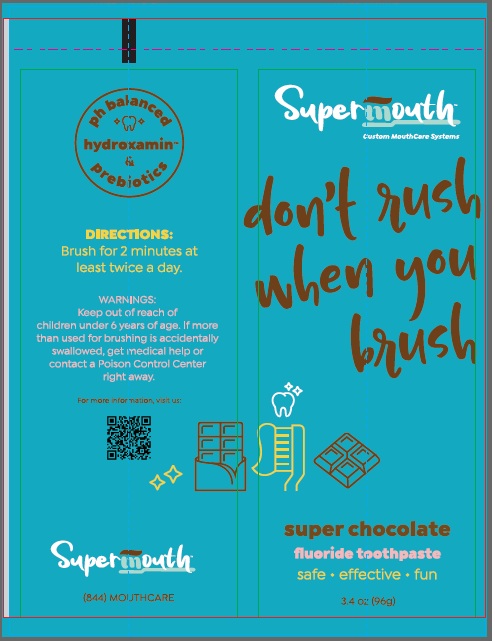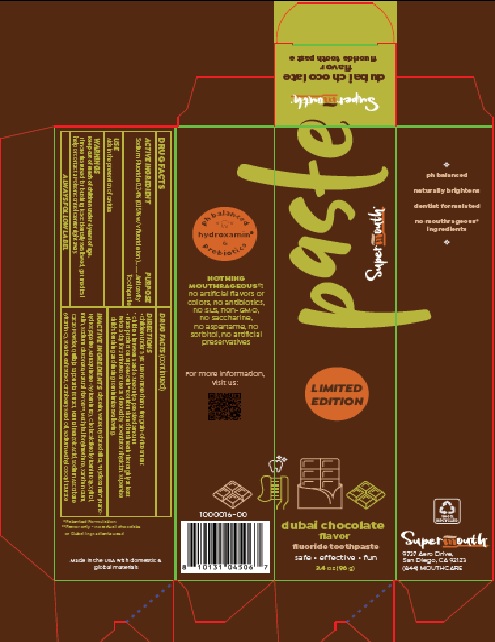 DRUG LABEL: Dubai Chocolate Flavor
NDC: 83729-119 | Form: PASTE, DENTIFRICE
Manufacturer: SuperMouth, LLC.
Category: otc | Type: HUMAN OTC DRUG LABEL
Date: 20250724

ACTIVE INGREDIENTS: SODIUM FLUORIDE 2.4 mg/1 g
INACTIVE INGREDIENTS: GLYCERIN; WATER; HYDRATED SILICA; TRIBASIC CALCIUM PHOSPHATE; MENAQUINONE 7; CHOLECALCIFEROL; XYLITOL; INULIN; SODIUM GLUCONATE; DIMETHYL SULFONE; XANTHAN GUM; COCOA; QUILLAJA SAPONARIA WHOLE; BENZOIC ACID; SODIUM ASCORBATE; STEVIA LEAF; CRANBERRY SEED OIL; SODIUM METHYL COCOYL TAURATE

Dubai Chocolate Flavor Toothpaste

DRUG FACTS

ACTIVE INGREDIENT

Sodium Fluoride 0.24% (0.15% w/v fluoride ion)

PURPOSE
Anticavity Toothpaste

USE

Aids in the prevention of cavities

WARNINGS

Keep out of reach of children under 6 years of age.

OTHER SAFETY INFORMATION

If more than used for brushing is accidentally swallowed, get medical help or
contact a Poison Control Center right away.

ALWAYS FOLLOW LABEL

DIRECTIONS

- Children under 3 yrs: use no more than a tiny grain-of-rice smear.

- Children between 3 and 6: use only a pea sized amount.

• Place product on SuperMouth® toothbrush and brush teeth thoroughly at least
twice a day for 2 minutes or use as directed by a Dentist or Physician. Supervise
child’s brushing and rinsing to minimize swallowing.

INACTIVE INGREDIENT

INACTIVE INGREDIENTS Glycerin, Water, Hydrated Silica, *Hydroxamin® (Nano-
Hydroxyapatite, Menaquinone-7 (Vitamin K2), Cholecalciferol (Vitamin D3)), Xylitol,
Inulin, Sodium Gluconate, Natural Flavors**, Methylsulfonylmethane, Xanthan Gum,
Cacao Powder, Quillaja Saponaria Extract, Natural Benzoic Acid, Sodium Ascorbate
(Vitamin C), Stevia Leaf Extract, Cranberry Seed Oil, Sodium Methyl Cocoyl Taurate

Product Labeling: Dubai Chocolate Flavor Toothpaste

..........................................................................

Supermouth

dubai chocolate

flavor

fluoride toothpaste

safe • effective • fun

3.4 oz (96 g)

SuperMouth®

9737 Aero Drive,
San Diego, CA 92123
(844) MOUTHCARE

Carton Label

Tube Label

res